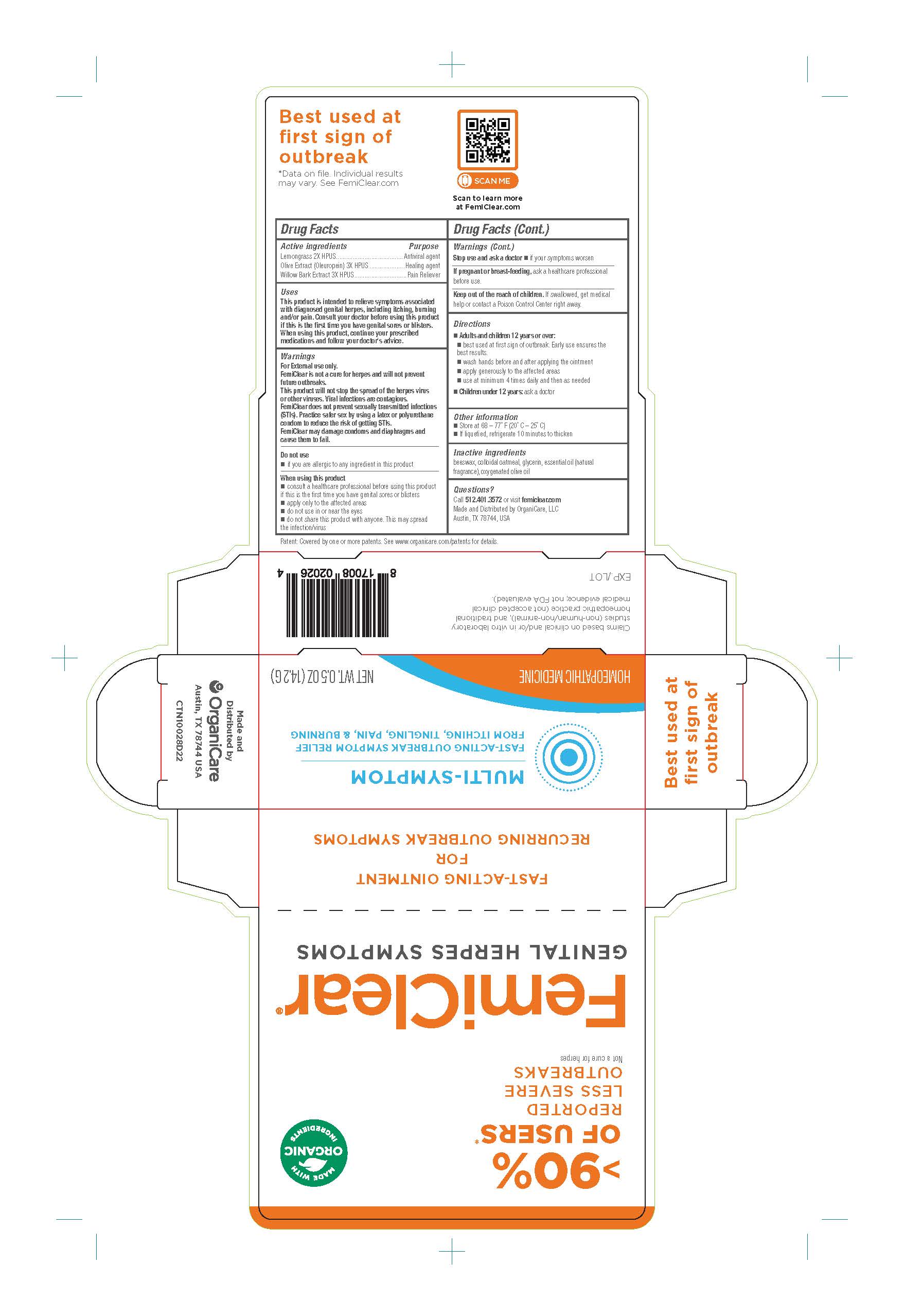 DRUG LABEL: FemiClear Genital Herpes Symptoms
NDC: 71042-024 | Form: OINTMENT
Manufacturer: Organicare Nature's Science, LLC
Category: homeopathic | Type: HUMAN OTC DRUG LABEL
Date: 20251020

ACTIVE INGREDIENTS: WILLOW BARK 3 [hp_X]/100 g; OLEA EUROPAEA FRUIT VOLATILE OIL 3 [hp_X]/100 g; EAST INDIAN LEMONGRASS OIL 2 [hp_X]/100 g
INACTIVE INGREDIENTS: OATMEAL; YELLOW WAX; OLIVE OIL; GLYCERIN

FemiClear Genital Herpese Symptoms (Multisymptom)

Active Ingredients

Lemongrass 2X HPUS

Olive Extract (Oleuropein) 3X HPUS

Willow Bark Extract 3X HPUS

Purpose

Antiviral agent

Healing agent

Pain Reliever

Uses

This product is intended to relieve symptoms associated with diagnosed genital herpes, including itching, burning and or pain. Consult your doctor before using this product if this is the first time you have genital sores or blisters. When using this product, continue your prescribed medications and follow your doctor's advice.

Warnings

For external use only.

FemiClear is not a cure for herpes and will not prevent future outbreaks.

This product will not stop the spread of the herpes viruses or other viruses. Viral infections are contagious.

FemiClear does not prevent other sexually transmitted infections (STIs). Practice safer sex by using latex or polyurethane condom to reduce risk of getting STIs.

FemiClear may damage condoms and diaphragms and cause ethem to fail

Do not use

if you are allergic to any ingredient in this product

When using this product

Consult a healthcare professional before using this product if this is the first time you have genital sores or blisters

apply only to affected areas

Do not use in or near the eyes

do not share this product with anyone. This may spread the infection/virus

Stop use and ask a doctor

if your symptoms worsen

If pregnant or breast-feeding

ask a healthcare professional before use.

Keep out of the reach of children

If swallowed, get medical help or contact Poison Control Center right away

Directions

Adults and children 12 years of age and older:

- best used at first sign of outbreak. Early use ensures the best results.
- wash hands before and after applying the ointment
- apply generously to the affected areas
- use at minimum 4 times daily and then as needed

Children under 12 years: ask a doctor

Inactve ingredients

Beeswax, colloidal oatmeal, glycerin, essential oil (natural fragrance), oxygenated olive oil

Questions?

Call 512.401.3572 or visit femiclear.com

Made and Distributed by OrganiCare, LLC

Austin, TX 78744, USA

Claims based on clinical and/or in vitro laboratory

(non-human/non-animal) studies, and traditional homeopathic practice (not accepted clinical medical evidence; not FDA evaluated).

Made and Distributed by

Organicare

Austin, TX 78744, USA

PACKAGE LABEL

FemiClear®

GENITAL HERPES SYMPTOMS

>90% OF USERS* REPORTED LESS SEVERE OUTBREAKS

Not a cure for herpes

MADE WITH ORGANIC INGREDIENTS

MULTI-SYMPTOM

FAST ACTING OUTBREAK SYMPTOM RELIEF FROM ITCHING, TINGLING, PAIN & BURNING